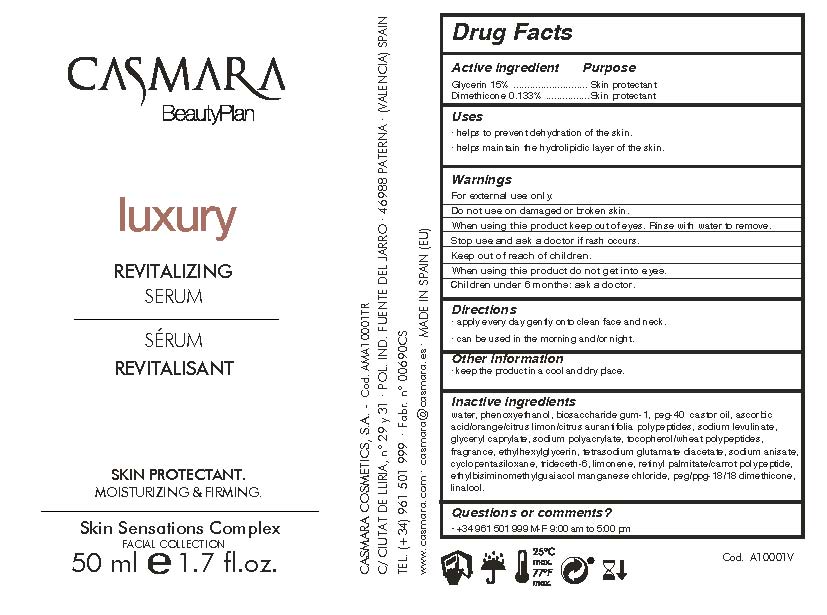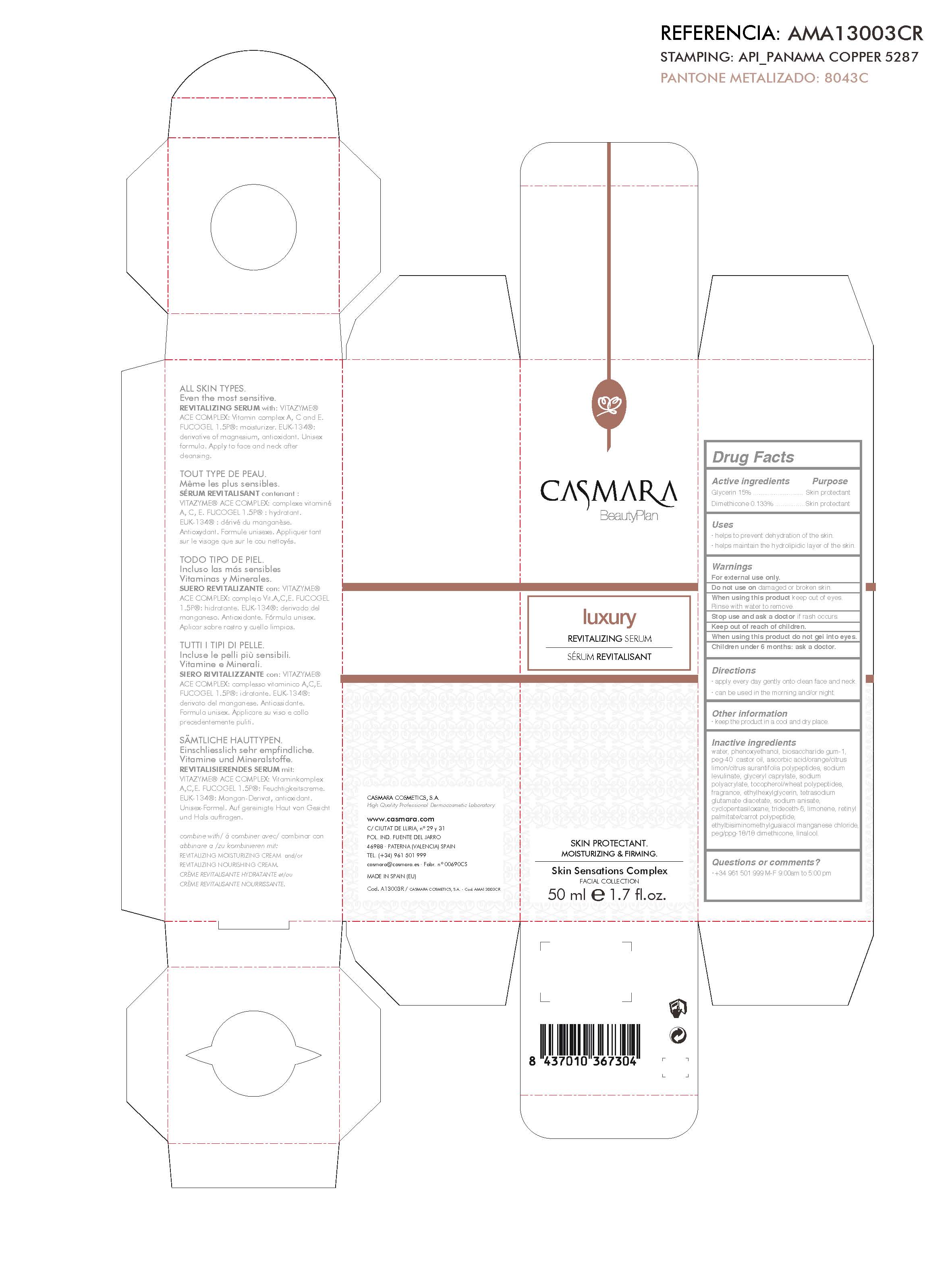 DRUG LABEL: Luxury Revitalizing Serum
NDC: 20151-063 | Form: CREAM
Manufacturer: CASMARA COSMETICS, SA
Category: otc | Type: HUMAN OTC DRUG LABEL
Date: 20161101

ACTIVE INGREDIENTS: GLYCERIN 15 mg/1 mL; DIMETHICONE 0.13 mg/1 mL
INACTIVE INGREDIENTS: SODIUM ANISATE 0.08 mg/1 mL; GLYCERYL CAPRYLATE 0.21 mg/1 mL; WATER 81.17 mg/1 mL; DIMETHICONE CROSSPOLYMER (450000 MPA.S AT 12% IN CYCLOPENTASILOXANE) 0.069 mg/1 mL; ETHYLHEXYLGLYCERIN 0.1 mg/1 mL; TETRASODIUM GLUTAMATE DIACETATE 0.094 mg/1 mL; PERFLUNAFENE 0.1 mg/1 mL; PHENOXYETHANOL 0.9 mg/1 mL; PEG-40 CASTOR OIL 0.5 mg/1 mL; LINALOOL, (+)- 0.006 mg/1 mL; BIOSACCHARIDE GUM-1 0.057 mg/1 mL; SODIUM LEVULINATE 0.288 mg/1 mL; .ALPHA.-TOCOPHEROL 0.13 mg/1 mL; TRIDECETH-6 0.042 mg/1 mL; LIMONENE, (+)- 0.03 mg/1 mL; ETHYLBISIMINOMETHYLGUAIACOL MANGANESE CHLORIDE 0.01 mg/1 mL; PEG/PPG-18/18 DIMETHICONE 0.007 mg/1 mL; ASCORBIC ACID 0.33 mg/1 mL; SODIUM POLYACRYLATE (8000 MW) 0.18 mg/1 mL; VITAMIN A PALMITATE 0.031 mg/1 mL

Luxury Revitalizing Serum

Uses

. helps to prevent dehydration of the skin.

. helps maintain the hydrolipidic layer of the skin

Uses

. helps to prevent dehydration of the skin

. helps maintain the hydrolipidic layer of the skin

Warnings

For external use only.

Do not use on damaged or broken skin.

When using this product keep our of the eyes. Rinse with water to remove.

Stop use and ask a doctor if rash occurs.

Keep out of reach of children.

Whhen using this product do not get into eyes.

Children under 6 months: as a doctor.

Keep out of reach of children.

Warnings

Stop use and ask a doctor if rash occurs.

Questions or comments?

(305) 777-0548 M-F 9:00 am to 5:00 pm

Directions

. apply every day gently onto clean face and neck.

. can be used in the morning and/or night.

Other information

. keep the product in a cool and dry place.

Inactive ingredients

water, phenoxyethanol, biosaccharide gum-1, PEG-40 castor oil, ascorbic acid, sodium levulinate, glyceryl caprylate, sodium polyacrylate, alpha-tocopherol, dimethicone, perflunafene, ethylhexylglycerin, tetrasodium glutamate diacetate, sodium anisate, cyplopentasiloxane, trideceth-6, limonene, Vitamin A- Palmitate, ethylbisiminomethylguaiacol manganase chloride, PEG-PPG 18/18 dimethicone, linalool.

Directions

. apply every day gently onto clean face and neck

. can be used in the morning and/or night

Active Ingredients Purpose

Glycerin 15%.................... Skin Protectant

Dimethicone 0.133%.........Skin Protectant

Luxury Revitalizing Serum

Luxury
Revitalizing Serum
Skin Protectant
Moisturizing & Firming

Principal Display Panel

Luxury Revitalizing Serum

Skin Protectant

Moisturizing & Firming